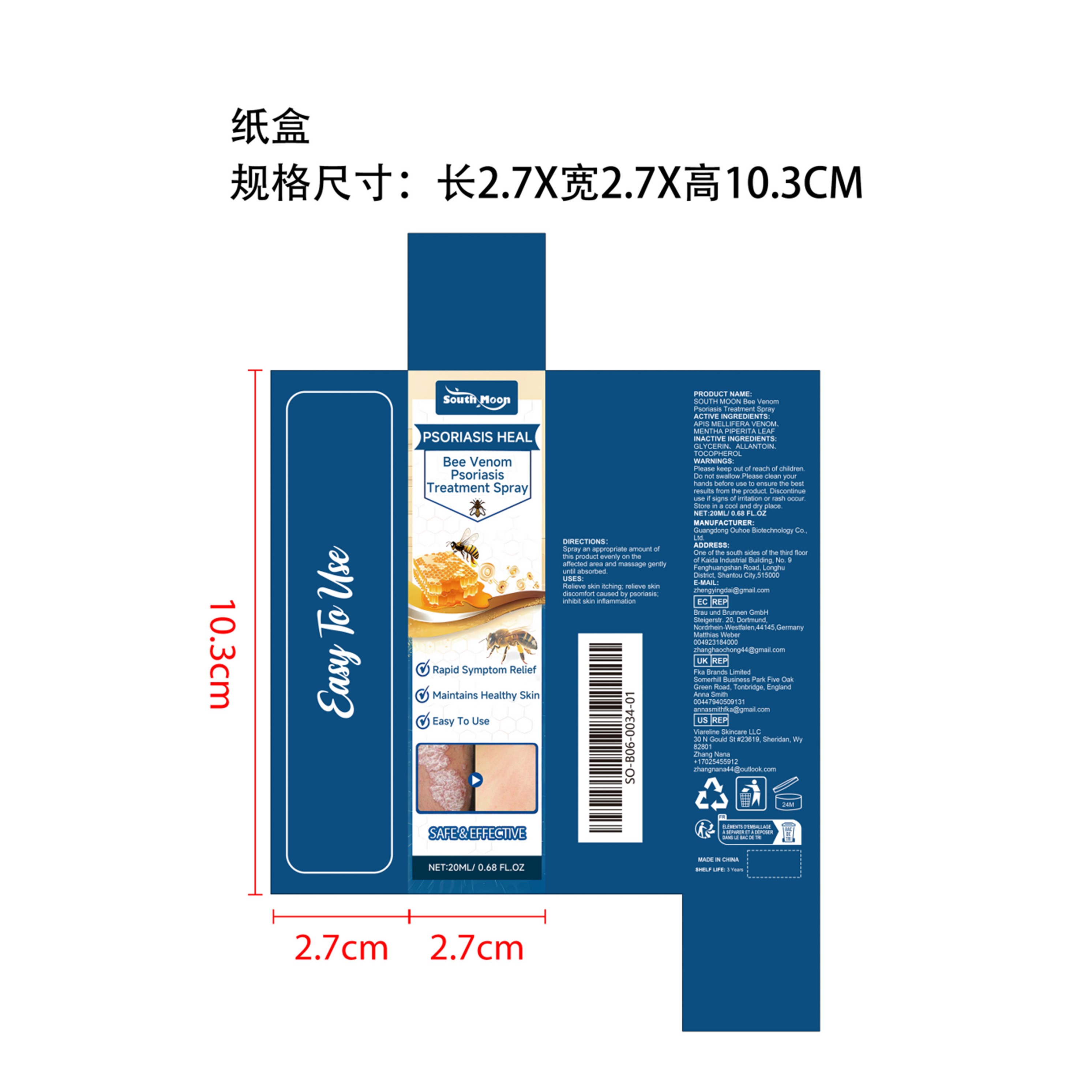 DRUG LABEL: South Moon Bee Venom Psoriasis Treatment
NDC: 84744-010 | Form: SPRAY
Manufacturer: Guangdong Ouhoe Biotechnology Co., Ltd.
Category: otc | Type: HUMAN OTC DRUG LABEL
Date: 20241016

ACTIVE INGREDIENTS: APIS MELLIFERA VENOM 2 g/100 g; MENTHA PIPERITA LEAF 7 g/100 g
INACTIVE INGREDIENTS: GLYCERIN; ALLANTOIN; TOCOPHEROL

Active Ingredient(s)

APIS MELLIFERA VENOM，MENTHA PIPERITA LEAF

Purpose

Quickly relieve psoriasis symptoms

Use

Relieve skin itching; relieve skin；discomfort caused by psoriasis;inhibit skin inflammation

Warnings

Please keep out of reach of children.Do not swallow.Please clean your hands before use to ensure the best results from the product.Discontinue use if signs of irritation or rash occur.Store in a cool and dry place.

Do not use

Discontinue use if signs of irritation or rash occur.

STOP USE

Discontinue use if signs of irritation or rash occur.

KEEP OUT OF REACH OF CHILDREN

Please keep out of reach of children. Do not swallow.

STORAGE AND HANDLING

Store in a cool and dry place.

INACTIVE INGREDIENT

GLYCERIN、 ALLANTOIN、 TOCOPHEROL